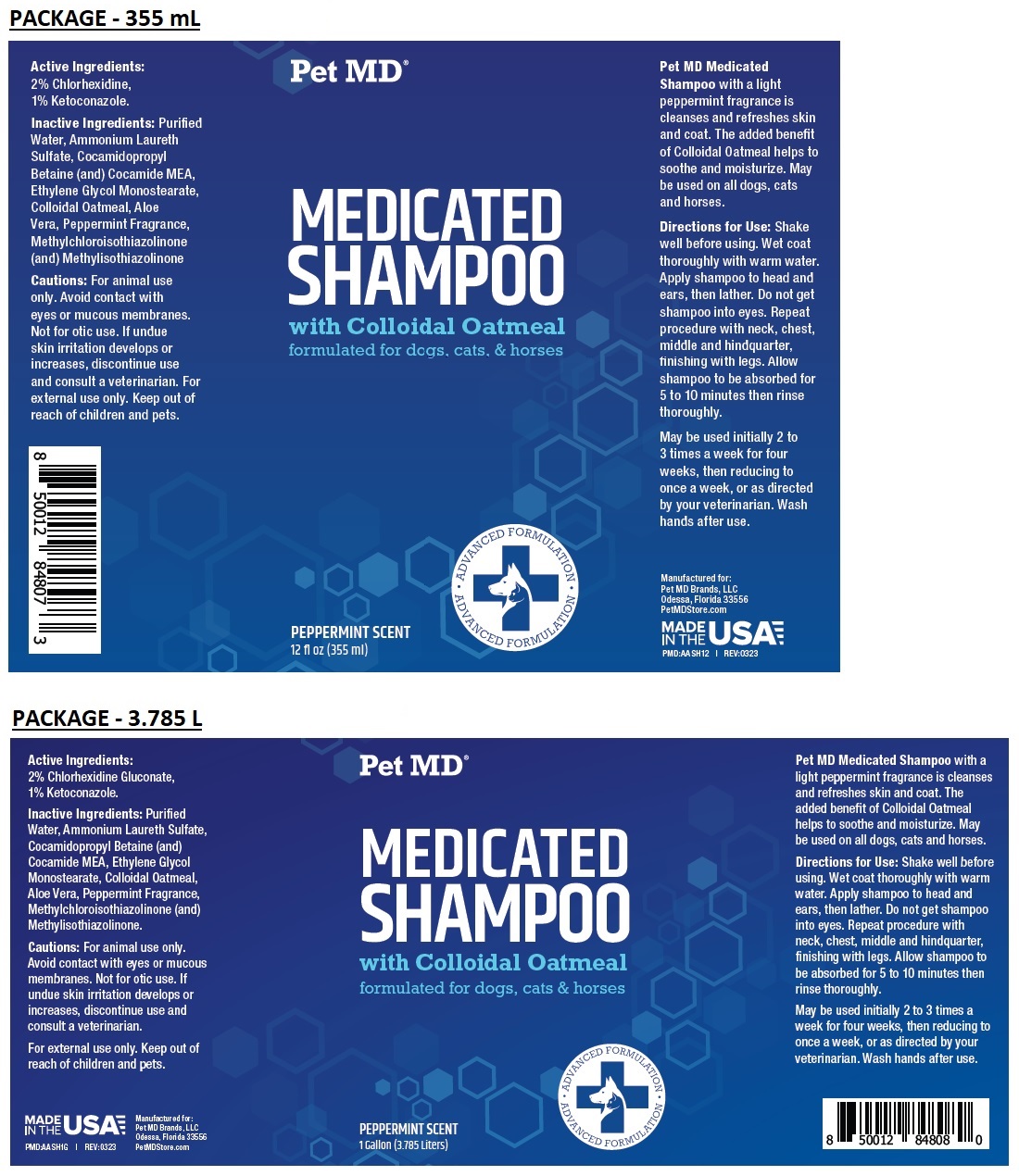 DRUG LABEL: Pet MD Medicated
NDC: 86090-014 | Form: SHAMPOO
Manufacturer: Pet MD Brands, LLC
Category: animal | Type: OTC ANIMAL DRUG LABEL
Date: 20230908

ACTIVE INGREDIENTS: CHLORHEXIDINE GLUCONATE 2 g/100 mL; KETOCONAZOLE 1 g/100 mL
INACTIVE INGREDIENTS: WATER; AMMONIUM LAURETH-3 SULFATE; COCAMIDOPROPYL BETAINE; COCO MONOETHANOLAMIDE; GLYCOL STEARATE; OATMEAL; ALOE VERA LEAF; PEPPERMINT; METHYLCHLOROISOTHIAZOLINONE; METHYLISOTHIAZOLINONE

Pet MD® MEDICATED SHAMPOO

Active Ingredients:

2% Chlorhexidine Gluconate,
1% Ketoconazole.

INDICATIONS AND USAGE

Pet MD Medicated Shampoo with a light peppermint fragrance is cleanses and refreshes skin and coat. The added benefit of Colloidal Oatmeal helps to soothe and moisturize. May be used on all dogs, cats and horses.

Inactive Ingredients:

Purified Water, Ammonium Laureth Sulfate, Cocamidopropyl Betaine (and) Cocamide MEA, Ethylene Glycol Monostearate, Colloidal Oatmeal, Aloe Vera, Peppermint Fragrance, Methylchloroisothiazolinone (and) Methylisothiazolinone.

Cautions:

For animal use only. Avoid contact with eyes or mucous membranes. Not for otic use. If undue skin irritation develops or increases, discontinue use and consult a veterinarian.
For external use only. Keep out of reach of children and pets.

Directions for Use:

Shake well before using. Wet coat thoroughly with warm water. Apply shampoo to head and ears, then lather. Do not get shampoo into eyes. Repeat procedure with neck, chest, middle and hindquarter, finishing with legs. Allow shampoo to be absorbed for 5 to 10 minutes then rinse thoroughly.
May be used initially 2 to 3 times a week for four weeks, then reducing to once a week, or as directed by your veterinarian. Wash hands after use.

with Colloidal Oatmeal

formulated for dogs, cats & horses

ADVANCED FORMULATION

PEPPERMINT SCENT

MADE IN THE USA

Manufactured for:
Pet MD Brands, LLC
Odessa, Florida 33556
PetMDStore.com